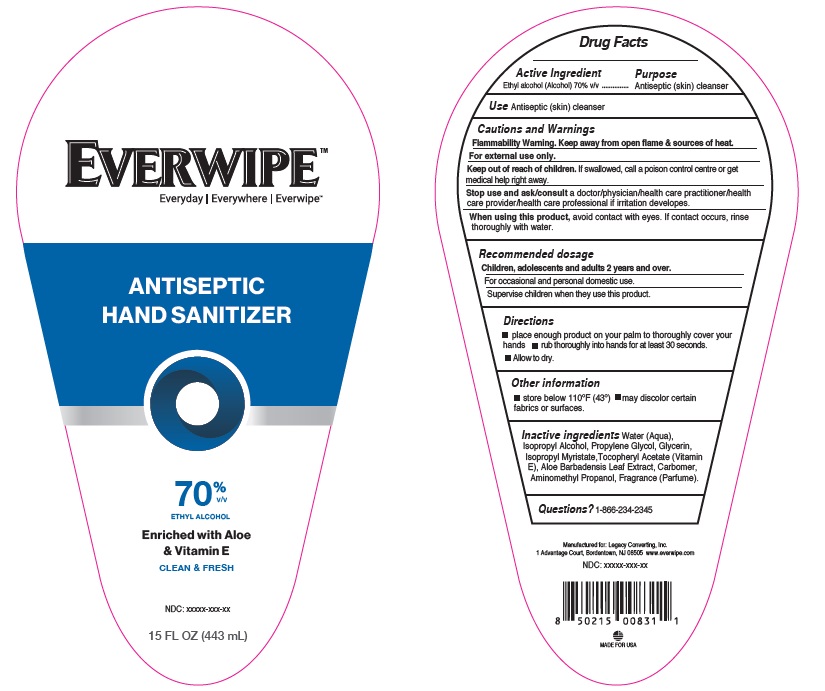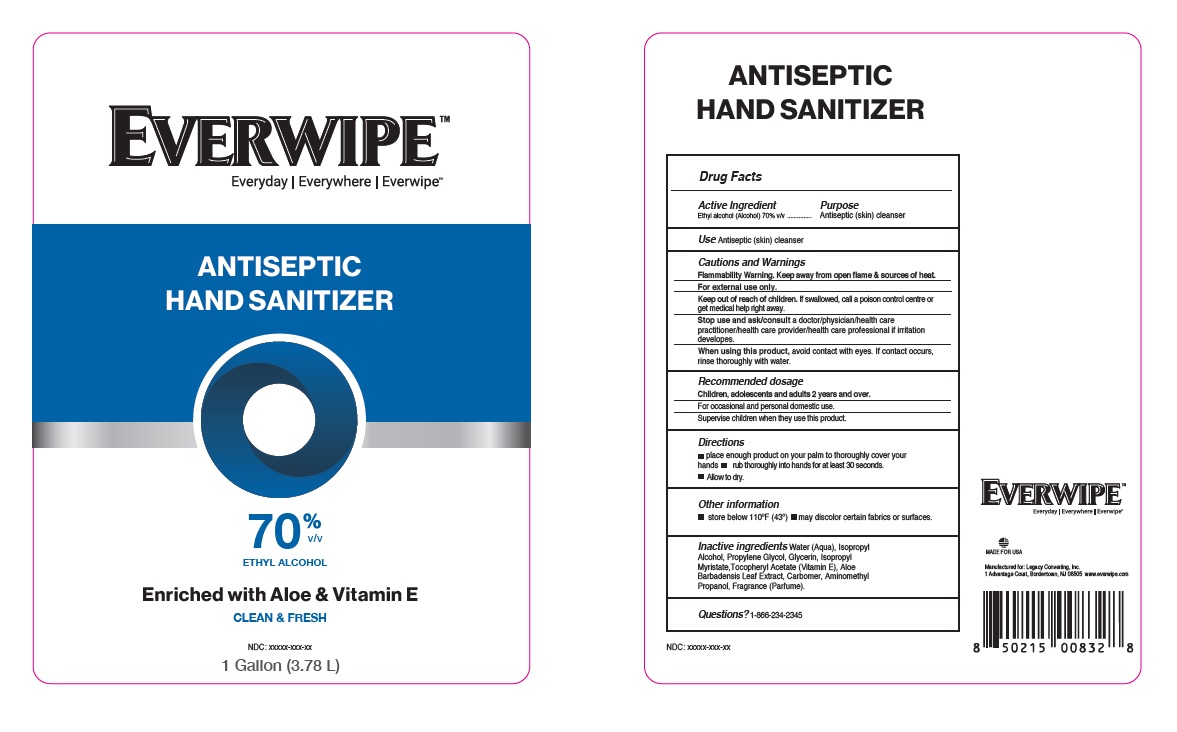 DRUG LABEL: Everwipe hand Sanitizer
NDC: 50157-518 | Form: GEL
Manufacturer: Brands International
Category: otc | Type: HUMAN OTC DRUG LABEL
Date: 20210311

ACTIVE INGREDIENTS: ALCOHOL 70 mL/100 mL
INACTIVE INGREDIENTS: ISOPROPYL MYRISTATE; WATER; PROPYLENE GLYCOL; CARBOMER INTERPOLYMER TYPE A (ALLYL SUCROSE CROSSLINKED); GLYCERIN; ALOE VERA LEAF; AMINOMETHYLPROPANOL; .ALPHA.-TOCOPHEROL ACETATE

Everwipe Hand sanitizer

Drug Facts

Active Ingredient

Ethyl Alcohol, 70% v/v

INDICATIONS AND USAGE

Antiseptic skin cleanser

Purpose

Antiseptic (skin) cleanser

Warnings

For external use only. Flammable, keep away from fire or flame.

When using this product.

- If contact occurs, rinse thoroughly with water.
- avoid contact with eyes.

Stop use and ask a doctor if irritation develops.

Keep out of reach of children. If swallowed, get medical help or contact a Poison Control Center right away.

Directions

- place enough product on your plam to thoroughly cover your hands
- rub thoroughly into hands for at least 30 seconds
- Allow to dry

Other Information

- Store below 43°C (110°F)
- may discolor certain fabrics or surfaces.

Inactive Ingredients

Carbomer, Aloe Barbadensis Leaf Extract, Aminomethyl Propanol, Glycerin, Propylene glycol, Water, Tocopheryl Acetate (Vit E).

Isopropyl Alcohol